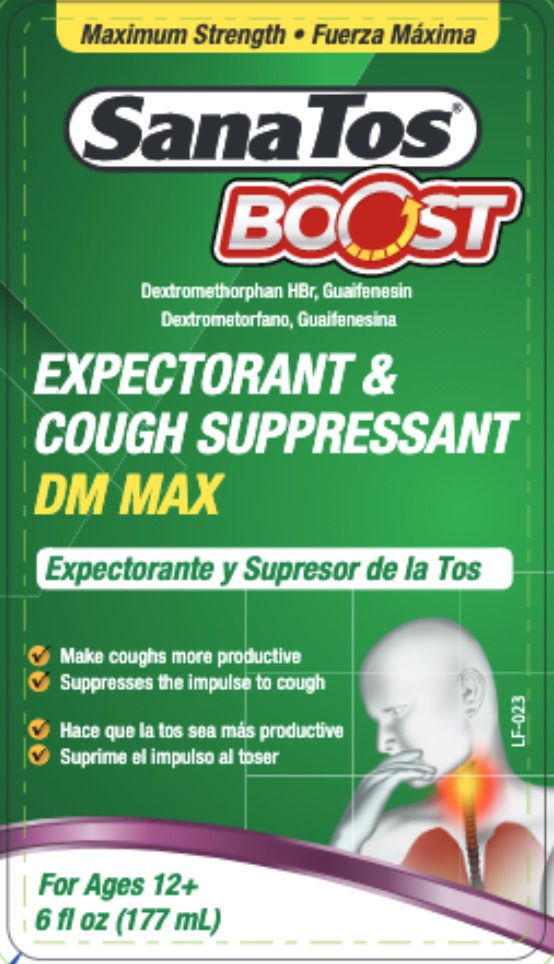 DRUG LABEL: SanaTos Boost
NDC: 55758-323 | Form: LIQUID
Manufacturer: Pharmadel LLC
Category: otc | Type: HUMAN OTC DRUG LABEL
Date: 20241118

ACTIVE INGREDIENTS: DEXTROMETHORPHAN HYDROBROMIDE 20 mg/100 mL; GUAIFENESIN 400 mg/100 mL
INACTIVE INGREDIENTS: DEXTROSE; WATER; ANHYDROUS CITRIC ACID; SACCHARIN SODIUM; GLYCERIN; FD&C RED NO. 40; MALTITOL; PROPYLENE GLYCOL; SUCRALOSE; SODIUM BENZOATE; XANTHAN GUM

SanaTos Boost DM MAX (Apta)

Active ingredients & Purposes

Active ingredient (in each 20 mL) | Purpose
Guaifenesin 400 mg............................................... | Expectorant
Dextromethorphan HBr 20 mg............................... | Cough suppressant

Uses

- helps loosen phlegm (mucus) and thin bronchial secretions to make coughs more productive
- temporarily relieves common cold/flu symptoms:
- cough due to minor throat and bronchial irritation

Warnings

Do not use

- for children under 12 years of age
- if you are now taking a prescription monoamine oxidase inhibitor (MAOI) (certain drugs for depression, psychiatric, or emotional conditions, or Parkinson's disease), or for two weeks after stopping the MAOI drug. If you do not know if your prescription drug contains an MAOI, ask a doctor or pharmacist before taking this product.

Ask a doctor before use if you have

- a persistent or chronic cough such occurs with smoking, asthma or emphysema
- trouble urinating due to an enlarged prostate gland

When using this product

- do not use more than directed

Stop use and ask a doctor if

- a persistent or chronic cough lasts for more than 7 days, tends to recur, or accompanied by fever, rash or persistent headache. These could be signs of a serious condition.

If pregnant or breast feeding,

ask a health professional before use.

Keep out of reach of children.

In case of overdose, get medical help or contact a Poison Control Center right away.

Directions

- do not exceed recommended dosage
- use dosage cup
- mL = milliliter
- do not take more than 6 doses in any 24-hour period

Age | Dose
adults & children 12 years and older | 20 mL every 4 hours
children under 12 years of age | do not use

Other information

- each 20 mL contains: sodium 12 mg
- use provided dosage cup
- store between 15-30°C (59-86°F)
- do not refrigerate

Inactive ingredients

anhydrous citric acid, dextrose, D&C red # 33, FD&C red #40, flavors, glycerin, maltitol, propylene glycol, saccharin sodium, sodium benzoate, sucralose, xanthan gum, water

Questions or comments?

+1-866-359-3478 (M-F) 9 AM to 5 PM Eastern or www.pharmadel.com

* This product is not manufactured or distributed by Reckitt Benckiser Inc.,
distributor of Mucinex® FAST-MAX TM DM MAX